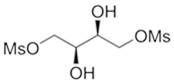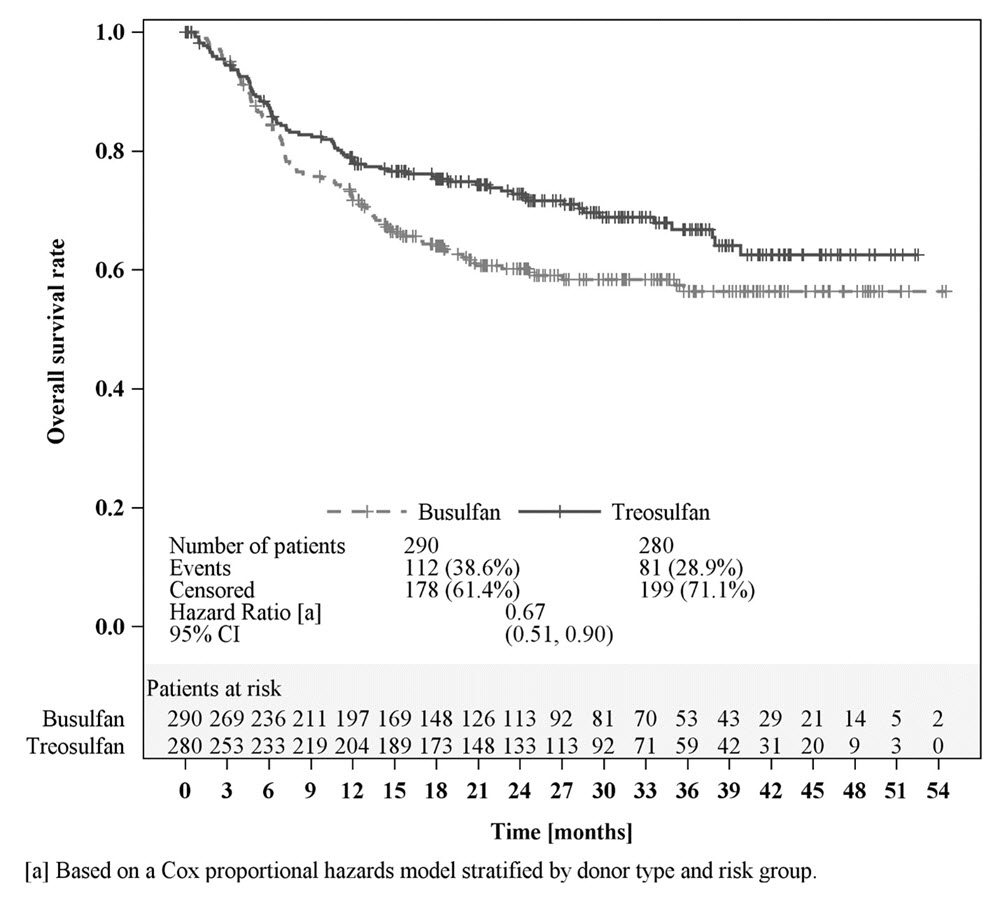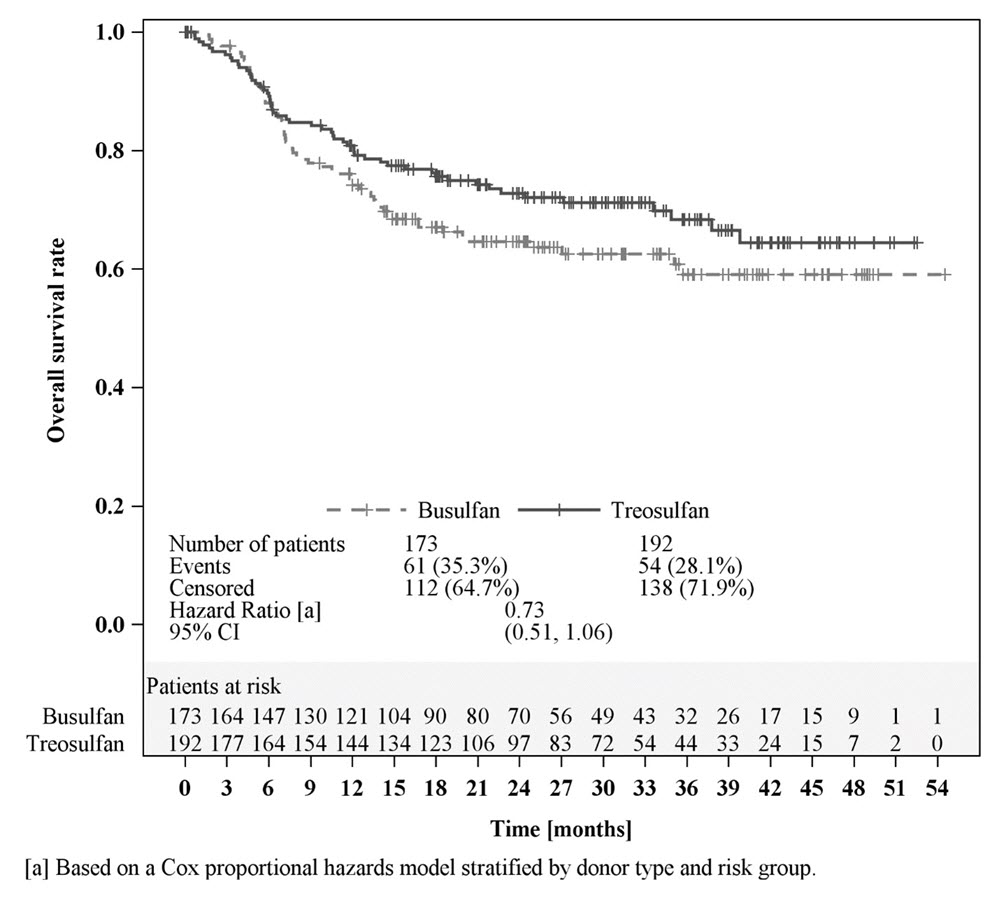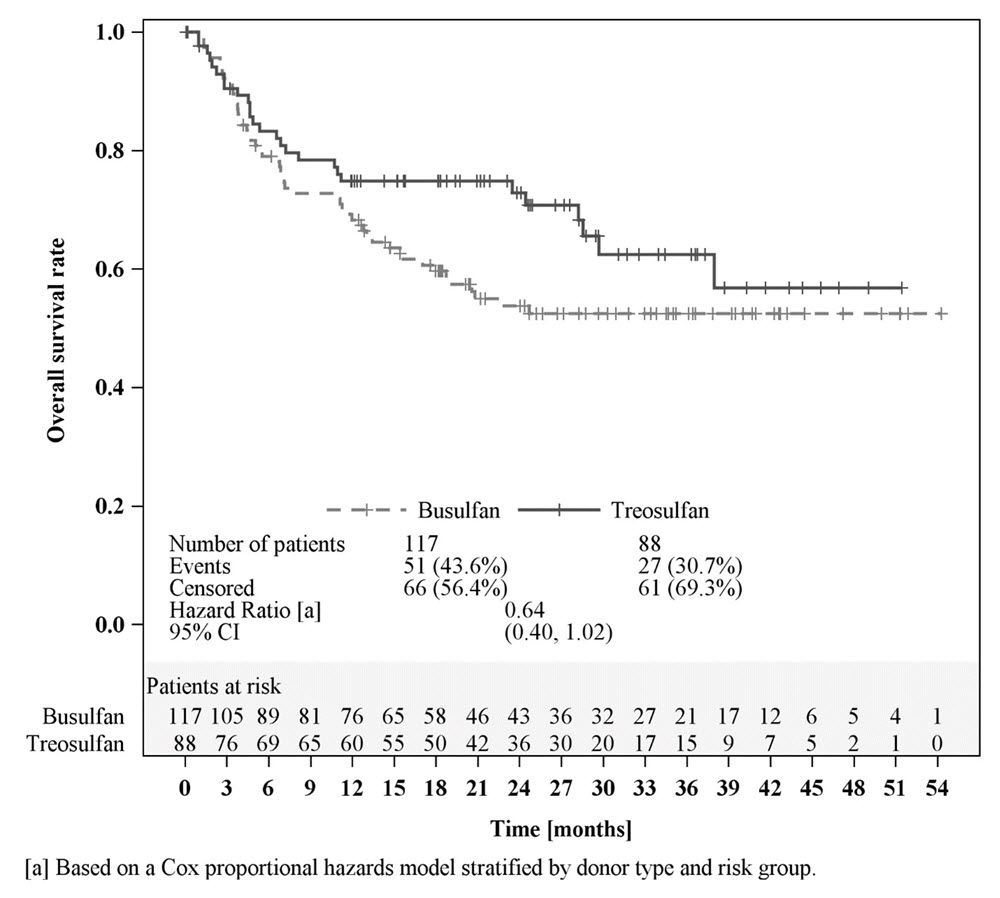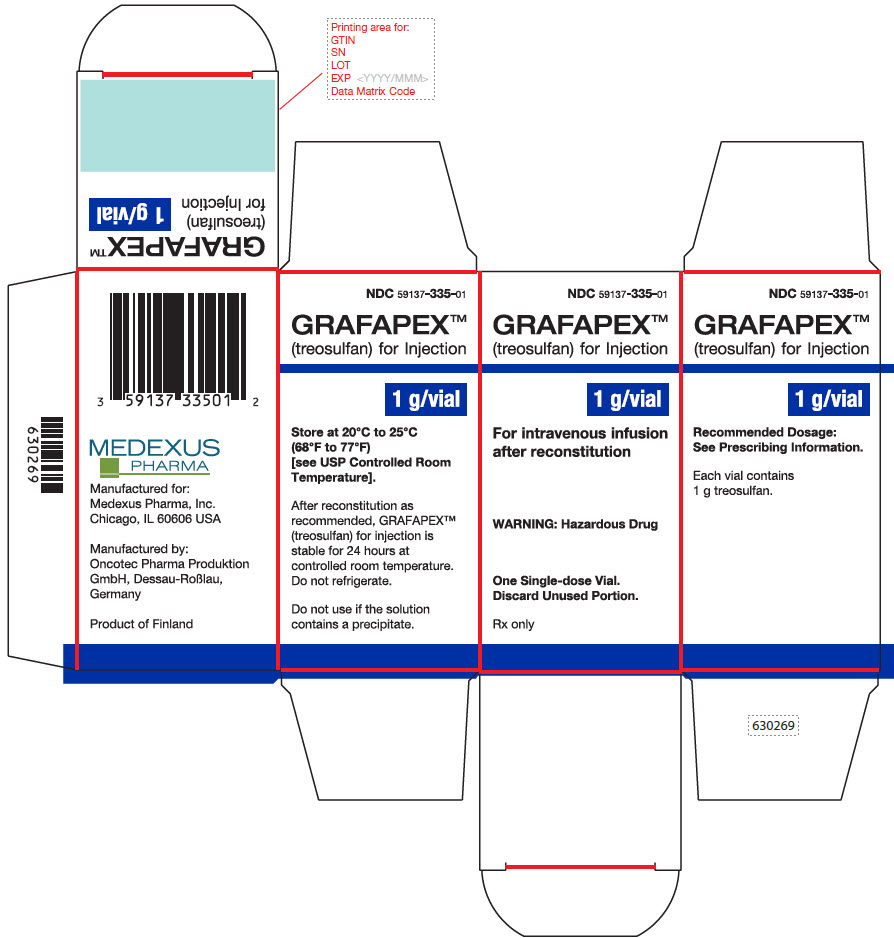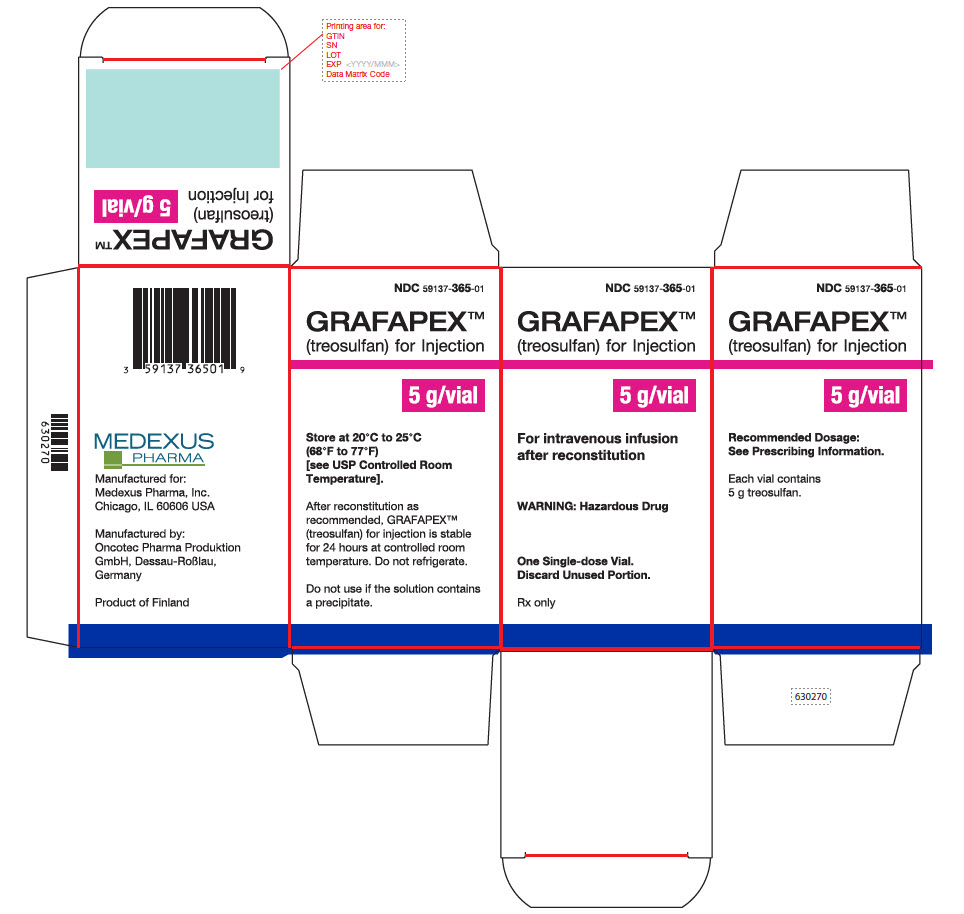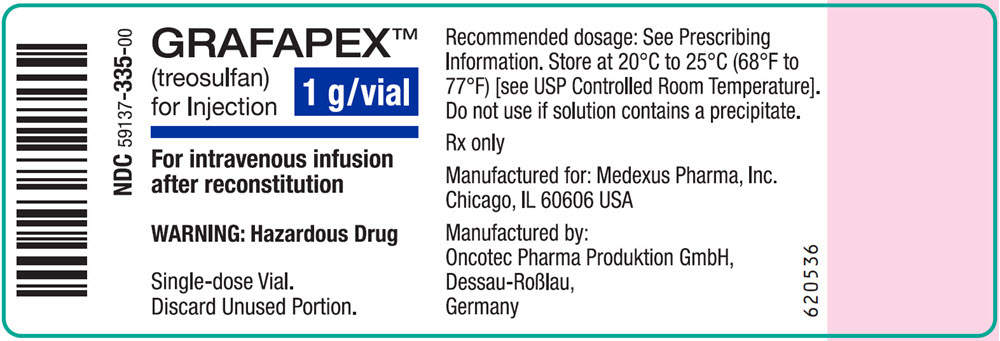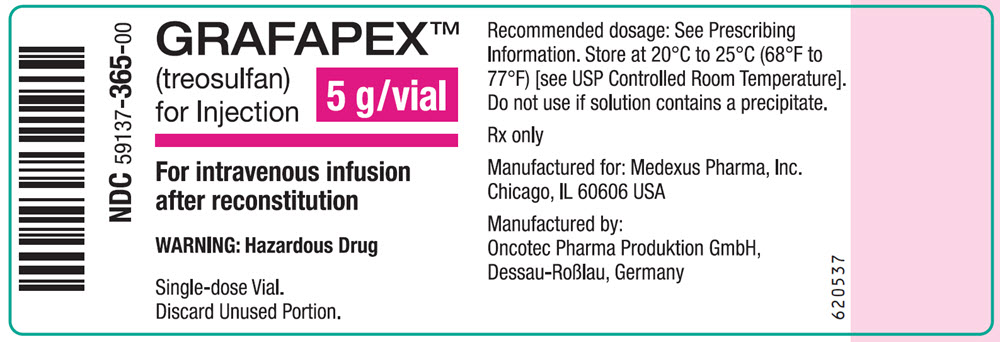 DRUG LABEL: GRAFAPEX
NDC: 59137-335 | Form: INJECTION, POWDER, LYOPHILIZED, FOR SOLUTION
Manufacturer: Medexus Pharma, Inc.
Category: prescription | Type: HUMAN PRESCRIPTION DRUG LABEL
Date: 20250131

ACTIVE INGREDIENTS: TREOSULFAN 1000 mg/1 g

HIGHLIGHTS OF PRESCRIBING INFORMATION

These highlights do not include all the information needed to use GRAFAPEX™ safely and effectively. See full prescribing information for GRAFAPEX.
GRAFAPEX (treosulfan) for injection, for intravenous use
Initial U.S. Approval: 2025

WARNING: MYELOSUPPRESSION

See full prescribing information for complete boxed warning.

- GRAFAPEX causes severe and prolonged myelosuppression.
- Hematopoietic stem cell transplantation is required to prevent potentially fatal complications of the prolonged myelosuppression. Monitor hematologic laboratory parameters. (5.1)

1 INDICATIONS AND USAGE

GRAFAPEX is an alkylating drug indicated for:

- Use in combination with fludarabine as a preparative regimen for allogeneic hematopoietic stem cell transplantation (alloHSCT) in adult and pediatric patients 1 year of age and older with acute myeloid leukemia (AML). (1.1).
- Use in combination with fludarabine as a preparative regimen for allogeneic hematopoietic stem cell transplantation in adult and pediatric patients 1 year of age and older with myelodysplastic syndrome (MDS). (1.2).

2 DOSAGE AND ADMINISTRATION

Recommended dosage: 10 g/m² body surface area (BSA) per day as a two hour intravenous infusion, given on three consecutive days (day -4, -3, -2) in conjunction with fludarabine before hematopoietic stem cell infusion (day 0). (2.1, 2.2)

- See Full Prescribing Information for instructions on preparation and administration. (2.2)

3 DOSAGE FORMS AND STRENGTHS

For injection: 1 g/vial and 5 g/vial treosulfan as a lyophilized powder in a single-dose vial. (3)

4 CONTRAINDICATIONS

- Hypersensitivity to any component of the drug product. (4)

5 WARNINGS AND PRECAUTIONS

- Seizures: Monitor signs of neurological adverse reactions and consider clonazepam prophylaxis for patients at higher risk. (5.2)
- Skin disorders: Keep skin clean and dry on days of GRAFAPEX infusion and change occlusive dressings after infusion. Change diapers frequently during the 12 hours after each infusion of GRAFAPEX. (5.3)
- Injection Site Reactions and Tissue Necrosis: May cause local tissue necrosis and injection site reactions, including erythema, pain, and swelling, in case of extravasation. If extravasation occurs, stop the infusion immediately and manage medically as required. (5.4)
- Secondary Malignancies: There is an increased risk of a secondary malignancy with use of GRAFAPEX. (5.5)
- Increased Early Morbidity and Mortality at Dosages Higher than Recommended: Avoid exceeding the recommended dosage of 10 g/m^2daily for three consecutive days. (5.6)
- Embryo-fetal toxicity: Can cause fetal harm. Advise patients of reproductive potential of the potential risk to a fetus and to use effective contraception. (5.7, 8.1, 8.3)

6 ADVERSE REACTIONS

The most common adverse reactions (≥20%) are musculoskeletal pain, stomatitis, pyrexia, nausea, edema, infection, and vomiting. (6.1) Selected Grade 3 or 4 nonhematological laboratory abnormalities are increased GGT, increased bilirubin, increased ALT, increased AST, and increased creatinine.

To report SUSPECTED ADVERSE REACTIONS, contact Medexus Pharma, Inc. at 1-855-336 -3322 or FDA at 1-800-FDA-1088 orwww.fda.gov/medwatch.

7 DRUG INTERACTIONS

- Certain CYP2C19 and CYP3A4 Substrates: Monitor for adverse reactions of these substrates where minimal concentration changes may lead to serious or life-threatening toxicities. (7.1)

8 USE IN SPECIFIC POPULATIONS

- Lactation: Advise not to breastfeed. (8.2)

FULL PRESCRIBING INFORMATION

WARNING: MYELOSUPPRESSION

- GRAFAPEX causes severe and prolonged myelosuppression at the recommended dosage.
- Hematopoietic stem cell transplantation is required to prevent potentially fatal complications of the prolonged myelosuppression. Monitor hematologic laboratory parameters [see Warnings and Precautions (5.1)] .

1 INDICATIONS AND USAGE

1.1 Acute Myeloid Leukemia

GRAFAPEX is indicated in combination with fludarabine as a preparative regimen for allogeneic hematopoietic stem cell transplantation in adult and pediatric patients 1 year of age and older with acute myeloid leukemia (AML).

1.2 Myelodysplastic Syndrome

GRAFAPEX is indicated in combination with fludarabine as a preparative regimen for allogeneic hematopoietic stem cell transplantation in adult and pediatric patients 1 year of age and older with myelodysplastic syndrome (MDS).

2 DOSAGE AND ADMINISTRATION

2.1 Recommended Dosage

The recommended dosage of GRAFAPEX is 10 g/m^2by intravenous infusion given daily for three days, beginning on Day -4 prior to transplantation in combination with fludarabine as outlined in Table 1.

Table 1: Dosage Regimen for GRAFAPEX-Based Allogeneic HSCT
Treatment | Day -6 | Day -5 | Day -4 | Day-3 | Day -2 | Day -1 | Day 0
GRAFAPEX 10 g/m^2/day intravenous infusion |  |  | X | X | X
Fludarabine 30 mg/m^2/day intravenous infusion | X | X | X | X | X
Allogeneic hematopoietic stem cell infusion |  |  |  |  |  |  | X

Premedicate patients with antiemetics prior to the first dose of GRAFAPEX and continue antiemetics on a fixed schedule through completion of treosulfan administration.

2.2 Preparation and Administration Instructions

Reconstitute GRAFAPEX prior to intravenous infusion.

GRAFAPEX is a hazardous drug. Follow applicable special handling and disposal procedures.^1

- Use aseptic technique to prepare GRAFAPEX.
- Calculate the dose, the total volume of reconstituted GRAFAPEX solution required, and the number of GRAFAPEX vials needed.
- Reconstitute each vial with 0.45% Sodium Chloride Injection, 0.9% Sodium Chloride Injection, 5% Dextrose Injection, or Sterile Water for Injection, in its original glass container using volumes described in Table 2 to obtain a final concentration of approximately 0.05 g/mL of GRAFAPEX. Reconstitution with Sterile Water for Injection alone is not recommended in children less than or equal to 12 years of age due to the resulting hypo-osmolarity of the final solution.

Table 2: Reconstitution Solution Volume
Strength | Volume
1 g/vial | 20 mL
5 g/vial | 100 mL

- Shake the vial(s) to dissolve.
- Inspect the reconstituted solution for discoloration and particulate matter. The reconstituted solution appears as a clear colorless solution. Solutions showing any sign of precipitation should not be used. In case that solubility issues occur, prolonged standing time or slight warming of the reconstituted solution (hand warm) may be useful.
- Determine the volume of 0.05 g/mL reconstituted solution needed based on the required dose. Reconstituted solutions of GRAFAPEX may be combined into a larger glass vial, ethylene-vinyl acetate (EVA) bag or polyolefin (PO) bag. Discard any unused portion left in the vial(s).

If not used immediately store reconstituted GRAFAPEX solution at room temperature 20°C to 25°C (68°F to 77°F) for up to 24 hours. Do not use if the solution contains a precipitate.

Do not refrigerate.

Infuse GRAFAPEX intravenously over 2 hours. Confirm patency of the intravenous line prior to infusion. Monitor for extravasation; if extravasation occurs, stop the infusion [see Warnings and Precautions (5.4)] .

3 DOSAGE FORMS AND STRENGTHS

For injection: 1 g/vial or 5 g/vial treosulfan as a white, sterile, lyophilized powder in single-dose vials for reconstitution.

4 CONTRAINDICATIONS

GRAFAPEX is contraindicated in patients with hypersensitivity to any component of the drug product.

5 WARNINGS AND PRECAUTIONS

5.1 Myelosuppression

Profound myelosuppression with pancytopenia is the desired therapeutic effect of GRAFAPEX-based preparative regimens, occurring in all patients. Time to neutrophil counts > 0.5 Gi/L occurred at a median of 18 days (range 7-42 days) after allogeneic hematopoietic stem cell transplantation in adult patients treated using GRAFAPEX in combination with fludarabine as the preparative regimen.

Do not begin the preparative regimen if the stem cell donor is not available. Monitor blood cell counts daily until hematopoetic recovery. Provide standard supportive care for infections, anemia and thrombocytopenia until there is adequate hematopoietic recovery.

5.2 Seizures

There have been reports of seizures in patients following treatment with treosulfan. Monitor patients for signs of neurological adverse reactions. Clonazepam prophylaxis may be considered for patients at higher risk for seizures, including infants.

5.3 Skin Disorders

An increase of skin disorders (e.g. rash, dermatitis) was observed when patients received sodium bicarbonate-containing hydration in the course of treosulfan infusion, potentially because of acceleration of the pH‑dependent formation of alkylating epoxides [see Adverse Reactions (6.1) and Clinical Pharmacology (12.1)]. Keep skin clean and dry on days of GRAFAPEX infusion. Diaper dermatitis may occur because of excretion of treosulfan in the urine. Change diapers frequently during the 12 hours after each infusion of GRAFAPEX. Dermatitis may occur under occlusive dressings; change occlusive dressings after each infusion of GRAFAPEX.

5.4 Injection Site Reactions and Tissue Necrosis

GRAFAPEX may cause local tissue necrosis and injection site reactions, including erythema, pain, and swelling, in case of extravasation. Assure venous access patency prior to starting GRAFAPEX infusion, and monitor the intravenous infusion site for redness, swelling, pain, infection, and necrosis during and after administration of GRAFAPEX. If extravasation occurs, stop the infusion immediately and manage medically as required. Do not administer by the intramuscular or subcutaneous routes.

5.5 Secondary Malignancies

There is an increased risk of a secondary malignancy with use of GRAFAPEX. Treosulfan is carcinogenic and genotoxic [see Nonclinical Toxicology (13.1)] .

The risk of secondary malignancy is increased in patients with Fanconi anemia and other DNA breakage disorders. The safety and efficacy of GRAFAPEX have not been established for patients with these disorders.

5.6 Increased Early Morbidity and Mortality at Dosages Higher than Recommended

In MC‑FludT.14/L Trial I (NCT00822393), 330 adult patients were randomized to treosulfan at 14 g/m^2/day (1.4 times the recommended dose) for three consecutive days or busulfan at 3.2 mg/kg/day for two days, in combination with fludarabine as a preparative regimen for allogeneic transplantation. This trial was discontinued early due to a higher incidence of early fatal and/or serious adverse reactions in patients receiving treosulfan. Avoid exceeding the recommended GRAFAPEX dosage of 10 g/m^2daily for three consecutive days.

5.7 Embryo-Fetal Toxicity

Based on its mechanism of action, GRAFAPEX can cause fetal harm when administered to a pregnant woman because it is genotoxic and affects dividing cells [see Clinical Pharmacology (12) and Nonclinical Toxicology (13)]. Advise pregnant women of the potential risk to the fetus. Advise females of reproductive potential to use effective contraception during treatment with GRAFAPEX and for 6 months following the last dose of GRAFAPEX. Advise males with female partners of reproductive potential to use effective contraception during treatment with GRAFAPEX and for 3 months after the last dose [see Use in Specific Populations (8.1) and (8.3)].

6 ADVERSE REACTIONS

The following clinically significant adverse reactions are described elsewhere in the labeling:

- Myelosuppression [see Warnings and Precautions (5.1)]
- Seizures [see Warnings and Precautions (5.2)]
- Skin Disorders [see Warnings and Precautions (5.3)]
- Injection Site Reactions and Tissue Necrosis [see Warnings and Precautions (5.4)]
- Secondary Malignancies [see Warnings and Precautions (5.5)]

6.1 Clinical Trials Experience

Because clinical trials are conducted under widely varying conditions, adverse reaction rates observed in the clinical trials of a drug cannot be directly compared to rates in the clinical trials of another drug and may not reflect the rates observed in practice.

MC‑FludT.14/L Trial II

The safety of GRAFAPEX was evaluated in 553 adult patients with AML and MDS in a randomized trial (MC‑FludT.14/L Trial II) comparing GRAFAPEX in combination with fludarabine to busulfan in combination with fludarabine as a preparative regimen for allogeneic hematopoietic stem cell transplantation. The patients were randomized to receive GRAFAPEX (n=270) 10 g/m² daily on day -4, -3 and -2 or to busulfan (n=283) 0.8 mg/kg every 6 hours on day -4 and -3 in combination with fludarabine 30 mg/m^2daily on day -6, -5, -4, -3 and -2, and hematopoietic stem cell transplantation on day 0 [see Clinical Studies (14)] .

Fatal regimen-related adverse reactions occurred within 30 days of transplantation in 1.9% of patients on the GRAFAPEX arm. All fatalities were due to pulmonary adverse reactions.

The most common adverse reactions (≥20%) in patients treated with GRAFAPEX were musculoskeletal pain, stomatitis, pyrexia, nausea, edema, infection, and vomiting. Selected Grade 3 or 4 nonhematological laboratory abnormalities were increased GGT, increased bilirubin, increased ALT, increased AST, and increased creatinine.

Table 3 shows the adverse reactions in Study MC‑FludT.14/L Trial II through transplant Day +30.

Table 3: Adverse Reactions in ≥10% of Patients through Transplant Day +30 in Study MC-FludT.14/L Trial II
Adverse Reaction* | All Grades |  | Grades 3 or 4
 | GRAFAPEX (N = 270) | Busulfan (N = 283) | GRAFAPEX (N = 270) | Busulfan (N = 283)
 | % | % | % | %
Musculoskeletal pain | 39 | 27 | 5 | 2
Stomatitis | 38 | 48 | 6 | 7
Pyrexia | 34 | 36 | 1 | 3
Nausea | 33 | 41 | 3 | 6
Edema | 29 | 18 | 0.7 | 1
Infection^1 | 23 | 18 | 12 | 6
Vomiting | 22 | 19 | 1 | 1
Rash | 17 | 13 | 1 | 1
Diarrhea | 17 | 18 | 1 | 1
Headache | 16 | 18 | 1 | 1
Febrile neutropenia | 15 | 11 | 15 | 11
Abdominal pain | 15 | 13 | 3 | 2
Hypertension | 14 | 21 | 8 | 10
Hemorrhage | 14 | 14 | 1 | 1
Fatigue | 13 | 15 | 1 | 0.4
Constipation | 12 | 12 | 0.4 | 0
Tachycardia | 10 | 5 | 1 | 2
Hepatotoxicity | 10 | 8 | 4 | 3
*Includes grouped terms
^1Includes fatalities: n=6 in the GRAFAPEX arm and n=2 in the busulfan arm
Grading is based on Common Terminology Criteria for Adverse Events version 4.03

Clinically relevant adverse reactions in <10% of patients who received GRAFAPEX included:

Neoplasms benign, malignant and unspecified (including cysts and polyps): second malignancy
Metabolism and nutrition disorders:
Decreased appetite, impaired glucose tolerance
Psychiatric disorders: Insomnia, confusional state, agitation
Nervous system disorders: Paresthesia, dizziness
Ear and labyrinth disorders: Vertigo
Cardiac disorders: Cardiac failure, pericardial effusion
Vascular disorders: Flushing, embolism, hypotension
Respiratory, thoracic and mediastinal disorders: Pneumonitis, pleural effusion, pharyngeal or laryngeal inflammation, dyspnea, cough, oropharyngeal pain, hiccups, dysphonia
Gastrointestinal disorders: Oral pain, gastritis, dyspepsia, dysphagia, abdominal distension, dry mouth
Skin and subcutaneous tissue disorders: Palmar plantar erythrodysesthesia syndrome, pruritus, erythema, dermatitis, skin hyperpigmentation, dry skin
Renal and urinary disorders: Acute kidney injury, hematuria, urinary tract pain
General disorders and administration site conditions: Chills, pain

Investigations: Weight decreased or increased, increase of C‑reactive protein

All patients treated with GRAFAPEX and fludarabine developed neutropenia, anemia, and thrombocytopenia. One patient on the GRAFAPEX arm had graft failure. Table 4 summarizes the selected nonhematological laboratory abnormalities in Study MC-FludT.14/L Trial II by treatment arm through Day +30 posttransplant.

Table 4. Selected Grades 3-4 Laboratory Abnormalities through Transplant Day +30 in Study MC-FludT.14/L Trial II
Laboratory Abnormality | GRAFAPEX N = 270 % | Busulfan N = 283 %
Gamma Glutamyl Transferase Increased | 16 | 28
Bilirubin Increased | 6 | 5
Alanine Aminotransferase Increased | 6 | 4
Aspartate Aminotransferase Increased | 4 | 1
Creatinine Increased | 3 | 0.7
Grading is based on Common Terminology Criteria for Adverse Events version 4.03

6.2 Postmarketing Experience

The following additional adverse reactions have been identified during post approval use of GRAFAPEX in preparative regimens prior to hematopoietic stem cell transplantation in adult and pediatric patients in other countries. As these reactions are reported voluntarily from a population of uncertain size, it is not always possible to reliably estimate their frequency or establish a causal relationship to drug exposure.

Metabolism and Nutrition Disorders: Acidosis
Nervous system disorders: Peripheral sensory neuropathy
Renal and urinary disorders: Renal failure
Immune system disorders: Hypersensitivity

7 DRUG INTERACTIONS

7.1 Effect of GRAFAPEX on Other Drugs

Certain CYP2C19 and CYP3A4 Substrates

Monitor for adverse reactions of certain CYP2C19 or CYP3A4 substrates where minimal concentration changes may lead to serious or life-threatening toxicities, and reduce the dosage, as needed, if recommended in the prescribing information of these substrates.

Treosulfan is a CYP2C19 and CYP3A4 inhibitor [see Clinical Pharmacology (12)] . Concomitant use of GRAFAPEX is predicted to increase the exposure of CYP2C19 and CYP3A4 substrates based on a mechanistic understanding of treosulfan metabolism, which may increase the risk of their adverse reactions.

8 USE IN SPECIFIC POPULATIONS

8.1 Pregnancy

Risk Summary

Based on its mechanism of action, GRAFAPEX can cause fetal harm when administered to a pregnant woman because it is genotoxic and affects dividing cells [see Clinical Pharmacology (12) and Nonclinical Toxicology (13)] . There are no available human clinical data on the use of treosulfan in pregnant women to support an estimation of a drug-associated risk. Specific embryo-fetal developmental toxicity studies with treosulfan in animals were not conducted. Advise pregnant women of the potential risk to a fetus [see Data].

In the U.S. general population, the estimated background risk of major birth defects is 2% – 4% and of miscarriage is 15% – 20% of clinically recognized pregnancies.

Data

Animal Data

Animal reproductive or developmental toxicity studies were not conducted with treosulfan. Treosulfan is genotoxic and is toxic to dividing cells, suggesting it can cause embryotoxicity and teratogenicity.

8.2 Lactation

Risk Summary

There is no data on the presence of treosulfan or its metabolites in human milk, the effects on the breastfed child, or on milk production. Because of the potential for serious adverse reactions in breastfed children, advise women not to breastfeed during treatment with GRAFAPEX and for 1 week after the last dose.

8.3 Females and Males of Reproductive Potential

Based on its mechanism of action, GRAFAPEX can cause fetal harm when administered to a pregnant woman [see Use in Specific Populations (8.1)].

Pregnancy Testing

Conduct pregnancy testing in females of reproductive potential within 7 days prior to initiating therapy with GRAFAPEX.

Contraception

Females

Advise females of reproductive potential to use effective contraception during and up to 6 months after treatment with GRAFAPEX.

Males

Because of the potential for genotoxicity, advise males with female partners of reproductive potential to use effective contraception during treatment with GRAFAPEX and for 3 months after the last dose [see Nonclinical Toxicology (13.1)]

Infertility

Based on findings in animal studies, GRAFAPEX can impair fertility in females and males, and may cause temporary or permanent infertility [see Nonclinical Toxicology (13.1)] .

8.4 Pediatric Use

The safety and efficacy of GRAFAPEX as part of a preparative regimen prior to allogeneic hematopoietic stem cell transplant in pediatric patients 1 year of age and older with AML or MDS have been established based on evidence from an adequate and well-controlled study in adults, with additional pharmacokinetic and safety data in 111 pediatric patients, including 22 infants (1 month to < 2 years), 54 children (2 to < 12 years), and 35 adolescents (12 to < 17 years) [see Adverse Reactions (6.1), Clinical Pharmacology (12.3), and Clinical Studies (14)] . The incidence of hepatic and gastrointestinal adverse reactions was higher in pediatric patients than in adults.

Safety and effectiveness of GRAFAPEX as part of a preparative regimen prior to allogeneic hematopoietic stem cell transplant in pediatric patients with AML or MDS younger than 1 year of age have not been established.

Juvenile Animal Toxicity Data

Treatment of juvenile rats from postnatal day (PND) 10 to 35 with daily doses of 10, 50 or 100 mg/kg treosulfan (approximately 0.006, 0.03, 0.06-‑fold the human dose based on body surface area, BSA) generally resulted in findings comparable to those seen in adult animals. A delayed physical development indicated by decreased body weight, reduced relative organs weights, and delayed time point of vaginal opening were noted in the high-dosed rats. In a separate study, single intravenous administrations of 500 mg/kg treosulfan (0.3-‑fold the human dose based on BSA) to juvenile (PND 10) and young adult (PND 34 – 35) rats, treosulfan concentrations in brain tissue were low compared to plasma concentrations, but were approximately 2- to 3-fold higher in juvenile rats (4-6%) in comparison to young adults (2-3%).

8.5 Geriatric Use

Of the total number of GRAFAPEX-treated patients with AML or MDS in Study MC-FludT.14/L Trial II (n=270), 73 (27%) were 65 to 74 years of age, and none were 75 years of age and older [see Clinical Studies (14)] . No significant differences in safety or effectiveness were observed between these subjects and younger subjects.

10 OVERDOSAGE

The principal toxic effect of treosulfan in cases of overdose are myeloablation and prolonged pancytopenia, mucositis, skin toxicity, nausea, vomiting and gastritis. In case of overdosage, monitor blood counts frequently and provide vigorous supportive measures as medically indicated.

11 DESCRIPTION

GRAFAPEX for injection contains treosulfan, an alkylating drug. Treosulfan is known chemically as L-‑threitol ‑1,4-‑dimethanesulfonate. Treosulfan is soluble in water (7% m/v) at 25ᴼC. Treosulfan is not hygroscopic.Treosulfan has the molecular formula C6H14O8S2and a molecular weight of 278.3 g/mole. Treosulfan has the following chemical structure:

GRAFAPEX is intended for intravenous administration. It is supplied as a white, sterile, lyophilized powder for injection in glass vials containing 1 g or 5 g treosulfan.

12 CLINICAL PHARMACOLOGY

12.1 Mechanism of Action

Treosulfan is an alkylating agent. DNA alkylation is thought to be responsible for the cytotoxic activities of treosulfan. Treosulfan showed hematopoietic stem cell depleting activity as well as immunosuppressive and antitumor activity in mouse models of leukemia.

12.2 Pharmacodynamics

Increase in treosulfan exposure was associated with an increased incidence of infection-related death. Treosulfan time course of pharmacodynamic response is unknown.

12.3 Pharmacokinetics

Treosulfan pharmacokinetic parameters were observed at the approved recommended dosage, unless otherwise specified.

Treosulfan is a prodrug. Treosulfan mean ± SD area under the curve (AUC) is 1,200 ± 211 hr mcg/mL. There was no dose accumulation.

Distribution

Treosulfan mean (CV%) volume of distribution is approximately 41 liters (CV%: 19%). Treosulfan does not bind to plasma albumin.

Elimination

Treosulfan mean (± standard deviation) terminal half-life is 1.7 ± 0.4 hours.

Metabolism

The pharmacologically inactive treosulfan is converted spontaneously under physiological conditions into the active monoepoxide intermediate (2S,3S)‑1,2‑epoxybutane‑3,4‑diol‑4‑methanesulfonate) and finally to active L‑diepoxibutane (2S,3S)‑1,2:3,4‑diepoxybutane).

Excretion

A median of 42% of the treosulfan dose is excreted unchanged in the urine within 24 hours, and 89% of this unchanged fraction is excreted within the first 8 hours after administration.

Specific Populations

No clinically significant differences in the pharmacokinetics of treosulfan based on sex, mild renal impairment (CLcr 60‑89 mL/min), or mild hepatic impairment (total bilirubin less than or equal to ULN with AST greater than ULN or total bilirubin greater than 1 to 1.5 times ULN with any AST). The effect of moderate or severe renal impairment, moderate or severe hepatic impairment, and age ≥ 65 years on treosulfan pharmacokinetics is unknown.

Pediatric Patients

Treosulfan exposure in pediatric patients with BSA < 0.7 m^2and with BSA 0.7 to < 1.1 m^2are 11% and 5% higher, respectively, compared to adults.

No clinically significant difference in treosulfan median terminal half‑life was observed between pediatric patients and adults. The median terminal half‑life of the active monoepoxide intermediate was 1.6 hrs in pediatric patients.

Drug Interaction Studies

In Vitro Studies

CYP Enzymes:Treosulfan is a CYP2D6 substrate and its monoepoxide intermediate is a CYP2C8 substrate. Treosulfan inhibits CYP2C19 and CYP3A4 (using midazolam as substrate), but does not inhibit CYP1A2, CYP2B6, CYP2C8, CYP2C9, CYP2D6, or CYP3A4 (using testosterone as substrate).

Transporter Systems: Treosulfan does not inhibit BCRP, BSEP, MATE1, OATP1B1, OATP1B3, OAT1, OAT3, OCT1, or OCT2.

13 NONCLINICAL TOXICOLOGY

13.1 Carcinogenesis, Mutagenesis, Impairment of Fertility

Carcinogenesis and Mutagenesis

No carcinogenicity study has been conducted. Treosulfan was mutagenic in the in vitro bacterial mutagenicity assay (Ames test) and clastogenic in the in vitro micronucleus assay in human lymphocytes.

No dedicated animal fertility studies were conducted. In a general toxicity study in rats, animals were treated with 5 or 50 mg/kg/day treosulfan orally for 7 months, 6 days a week. Spermatogenesis and ovarian function were significantly affected, starting at 5 mg/kg (0.003‑fold the human dose based on BSA). Findings included reduced weight of the testicles, seminal vesicle, prostate, and uterus, as well as spermatogenesis reduction and arrest, uterine atrophy, and reduced or absent corpora lutea and follicles.

14 CLINICAL STUDIES

The efficacy of GRAFAPEX was evaluated in a randomized active-controlled trial (MC‑FludT.14/L Trial II; NCT00822393) comparing GRAFAPEX to busulfan in combination with fludarabine as a preparative regimen for allogeneic transplantation. Eligible patients included adults 18 to 70 years old with acute myeloid leukemia (AML) or myelodysplastic syndrome (MDS), Karnofsky performance status > 60%, and age ≥ 50 years or hematopoietic cell transplantation comorbidity index [HCT‑CI] score > 2. Patients were excluded if the creatinine clearance was < 60 mL/min, forced expiratory volume (FEV1) < 50% or on supplemental oxygen, left ventricular ejection fraction (LVEF) < 40%, bilirubin > 3X ULN, or aminotransferases (ALT or AST) > 5X ULN.

The patients were randomized to receive GRAFAPEX 10 g/m² daily on day -4, -3 and -2 or to busulfan 0.8 mg/kg every 6 hours on day -4 and -3 in combination with fludarabine 30 mg/m^2daily on day -6, -5, -4, -3 and -2, and hematopoietic stem cell transplantation on day 0. For the subset of patients with unrelated donors, antithymocyte globulin was administered in 97% and 95% of patients on each arm, respectively. Cyclosporine and methotrexate was used as graft‑vs‑host disease prophylaxis.

There were 570 patients randomized to GRAFAPEX (n = 280) or busulfan (n = 290). The efficacy population included 365 patients with AML and 205 patients with MDS: 536 patients received peripheral blood stem cells, 15 patients received marrow stem cells, and 19 patients were not transplanted. Table 5 shows the baseline characteristics of the study patients.

Table 5: Baseline characteristics of the study patients (MC‑FludT.14/L Trial II)
Baseline Characteristics | GRAFAPEX (n = 280) | Busulfan (n = 290)
Age, median (range), years | 60.0 (37, 70) | 60.5 (31, 70)
Age, n (%); - 18-64 years - 65-70 years | 204 (73%); 76 (27%) | 218 (75%); 72 (25%)
Gender, n (%); - Male - Female | 171 (61%) 109 (39%) | 176 (61%) 114 (39%)
Weight, median (range), kg | 80.0 (48.0, 144.0) | 78.1 (46.0, 141.9)
Disease, n (%); AML; MDS | 192 (69%); 88 (31%) | 173 (60%); 117 (40%)
AML remission status, n (%); - CR1 - >CR1 | 164 (85%); 28 (15%) | 148 (86%); 25 (14%)
MDS risk group, n (%); - Lower risk - Higher risk | 20 (23%); 68 (77%) | 20 (17%); 97 (83%)
HCT‑CI score; - ≤2 - >2 | 116 (41%); 164 (59%) | 118 (41%); 172 (59%)
Donor; - Matched related - Matched unrelated | 66 (24%); 214 (76%) | 68 (23%); 222 (77%)
Abbreviations: AML: acute myeloid leukemia; MDS: myelodysplastic syndrome; CR1: complete remission 1; HCT-CI: hematopoietic cell transplant-specific comorbidity index

Efficacy was established on the basis of overall survival (OS), defined as the time from randomization until death from any cause. The hazard ratio (HR) for OS (stratified by donor type and risk group) compared to busulfan was 0.67 (95% CI: 0.51, 0.90) in the randomized population, 0.73 (95% CI: 0.51, 1.06) in patients with AML, and 0.64 (95% CI: 0.40, 1.02) in patients with MDS. Results are displayed in Figures 1, 2, and 3 below.

Figure 1: Kaplan-Meier estimates of overall survival since time of randomization MC FludT.14/L Trial II

Figure 2: Kaplan-Meier estimates of overall survival since time of randomization MC FludT.14/L Trial II (patients with AML)

Figure 3: Kaplan-Meier estimates of overall survival since time of randomization MC FludT.14/L Trial II (patients with MDS)

15 REFERENCES

1. “OSHA Hazardous Drugs.” OSHA. http://www.osha.gov/SLTC/hazardousdrugs/index.html

16 HOW SUPPLIED/STORAGE AND HANDLING

How Supplied

GRAFAPEX (treosulfan) for injection is a white, sterile, lyophilized powder for reconstitution. It is supplied in a carton containing one single-dose vial.

Presentation | NDC
1 g/vial | 59137-335-01
5 g/vial | 59137-365-01

Storage and Handling

Store at 20°C to 25°C (68°F to 77°F) [see USP Controlled Room Temperature]. (Excursions permitted between 15°C and 30°C)

GRAFAPEX is a hazardous drug. Follow applicable special handling and disposal procedures^1.

17 PATIENT COUNSELING INFORMATION

Infections

- Inform patients of the increased risk of infections after treatment with GRAFAPEX that may require antibiotic, antiviral, or antifungal treatment and hospitalization.
- Advise patients to contact their healthcare provider immediately in case of any new or worsening signs of infection, e.g., cough, headache, diarrhea, or fever [see Warnings and Precautions (5.1)] .

Seizures

- Inform patients that seizures may occur [see Warnings and Precautions (5.2)] .

Skin Disorders

- Advise patients to clean “sweaty” skin parts (armpit, groin, genital area, inframammary line), each with a disposable washcloth and clear water.
- Advise patients not to apply any cream to the skin on the days of chemotherapy, and clothing should not be too tight, in order to let the skin “breathe” [see Warnings and Precautions (5.3)] .

Secondary Malignancies

- Inform patients of the possible risk of a second malignancy [see Warnings and Precautions (5.5)] .

Embryo-Fetal Toxicity

- Advise females of reproductive potential of the potential risk to a fetus and to inform their healthcare provider of a known or suspected pregnancy [see Use in Specific Populations (8.1)] .
- Advise females of reproductive potential to use effective contraception during treatment with GRAFAPEX and for 6 months following the last dose of GRAFAPEX [see Warnings and Precautions (5.7) and Use in Specific Populations (8.3)] .
- Advise males with female partners of reproductive potential to use effective contraception during treatment with GRAFAPEX and for 3 months after the last dose [see Warnings and Precautions (5.7) and Use in Specific Populations (8.3)] .

Lactation

- Advise women not to breastfeed during treatment with GRAFAPEX and for 1 week after the last dose [see Use in Specific Populations (8.2)].

Infertility

- GRAFAPEX can impair fertility in females and males, and may cause temporary or permanent infertility [see Use in Specific Populations (8.3)] .

Manufactured for:
Medexus Pharma, Inc.
Chicago, Illinois 60606
USA

GRAFAPEX™ is a trademark of medac GmbH, Germany.

PRINCIPAL DISPLAY PANEL - GRAFAPEX™ 1 g

Carton Label - GRAFAPEX™ 1 g

NDC 59137- 335-01

GRAFAPEX™
(treosulfan) for injection
1 g/vial

For intravenous infusion
after reconstitution

WARNING: Hazardous Drug

One Single-dose Vial.
Discard Unused Portion.

Rx only

One Single-dose Vial

Vial Label - GRAFAPEX™ 1 g

NDC59137 -335-00

GRAFAPEX™
(treosulfan)
for injection
1 g/vial

For intravenous infusion
after reconstitution

WARNING: Hazardous Drug

Single-dose Vial.
Discard Unused Portion.

Recommended dosage: See Prescribing
Information. Store at 20°C to 25°C (68°F to
77°F) [see USP Controlled Room Temperature].
Do not use if solution contains a precipitate.

Rx only

Manufactured for: Medexus Pharma, Inc.
Chicago, IL 60606 USA

Manufactured by:
Oncotec Pharma Produktion GmbH,
Dessau-Roβlau,
Germany

PRINCIPAL DISPLAY PANEL - GRAFAPEX™ 5 g

Carton Label - GRAFAPEX™ 5 g

NDC59137- 365-01

GRAFAPEX™
(treosulfan) for injection
5 g/vial

For intravenous infusion
after reconstitiution

WARNING: Hazardous Drug

One Single-dose Vial.
Discard Unused Portion.

Rx only

Vial Label - GRAFAPEX™ 5 g

NDC59137- 365-00
GRAFAPEX™
(treosulfan)
for injection
5 g/vial

For intravenous infusionafter reconstitution

WARNING: Hazardous Drug

Single-dose Vial.
Discard Unused Portion.

Recommended dosage: See Prescribing
Information. Store at 20°C to 25°C (68°F to
77°F) [see USP Controlled Room Temperature].
Do not use if solution contains a precipitate.

Rx only

Manufactured for: Medexus Pharma, Inc.
Chicago, IL 60606 USA

Manufactured by:
Oncotec Pharma Produktion GmbH,
Dessau-Roβlau, Germany